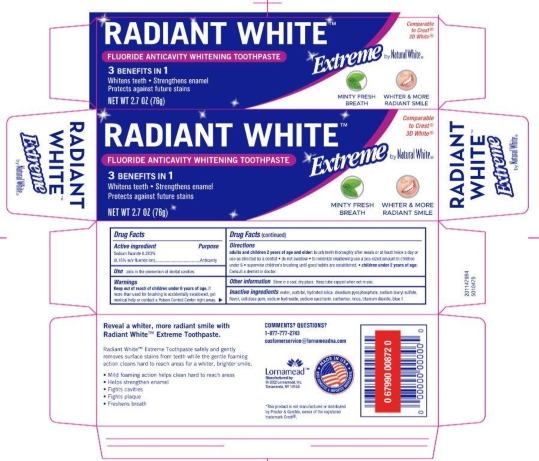 DRUG LABEL: Natural White
NDC: 62721-0473 | Form: PASTE, DENTIFRICE
Manufacturer: Lornamead
Category: otc | Type: HUMAN OTC DRUG LABEL
Date: 20250117

ACTIVE INGREDIENTS: SODIUM FLUORIDE 0.15 g/100 g
INACTIVE INGREDIENTS: POLYETHYLENE GLYCOL, UNSPECIFIED; WATER; SACCHARIN SODIUM; SORBITOL; TITANIUM DIOXIDE; SODIUM HYDROXIDE; XANTHAN GUM; HYDRATED SILICA; SODIUM ACID PYROPHOSPHATE; CARBOXYMETHYLCELLULOSE SODIUM, UNSPECIFIED FORM; CARBOMER HOMOPOLYMER TYPE B (ALLYL PENTAERYTHRITOL CROSSLINKED); SODIUM LAURYL SULFATE; MICA; FD&C BLUE NO. 1

5010479 NW Radiant White

Drug Facts

Active ingredient

Sodium fluoride 0.243%

Purpose

Anticavity

INDICATIONS AND USAGE

Use aids in the prevention of dental cavities

Warnings

Keep out of reach of children. If more than used for brushing is accidentally swallowed, get medical help or contact a Poison Control Center right away.

Directions

Adults and children 2 years of age and older: brush teeth thorughly preferably after each meal or at least twice a day, or as directed by a dentist or doctor.

- Instruct children under 6 years of age in good brushing and rinsing habits (to avoid swallowing).
- Supervise children as necessary until capable of using without supervision.
- Children under 12 years of age: consult a dentist or a doctor.

INACTIVE INGREDIENT

Inactive ingredients water, sorbitol, hydrated silica, disodium pyrophosphate, sodium lauryl sulfate, flavor, cellulose gum, xanthan gum, carbomer, sodium saccharin, sodium hydroxide, mica, titanium dioxide, blue 1 lake, polyethylene

Questions or comments? CALL 1-877-777-2743

Comments? Questions?

1-877-777-2473

customerservice@lornamead.com

Lornamead™

Manufactured by:

Lornamead, Inc.

Tonawanda, NY 14150

MADE IN USA